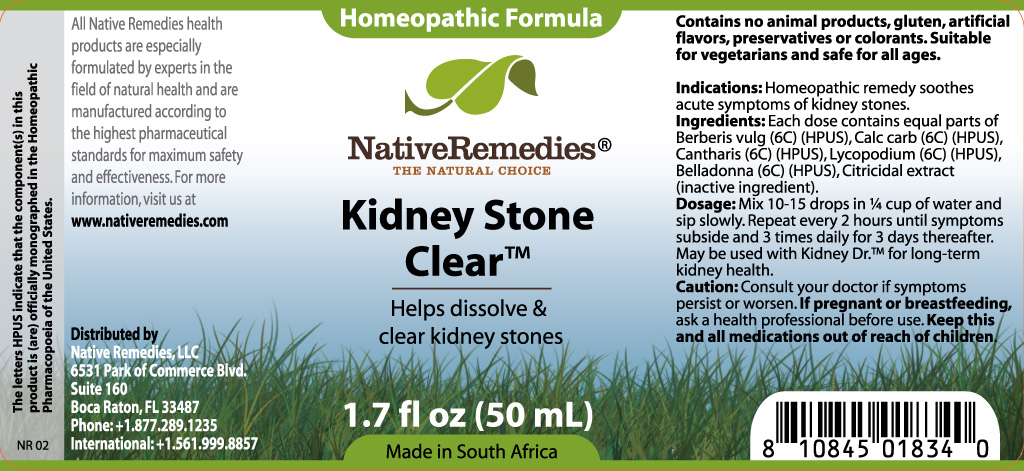 DRUG LABEL: Kidney Stone Clear
NDC: 50048-012 | Form: TINCTURE
Manufacturer: W. Last CC
Category: homeopathic | Type: HUMAN OTC DRUG LABEL
Date: 20111122

ACTIVE INGREDIENTS: BERBERIS VULGARIS FRUIT 6 [hp_C]/40 mL; CALCIUM CARBONATE 6 [hp_C]/40 mL; LYTTA VESICATORIA 6 [hp_C]/40 mL; LYCOPODIUM CLAVATUM SPORE 6 [hp_C]/40 mL; ATROPA BELLADONNA 6 [hp_C]/40 mL
INACTIVE INGREDIENTS: CITRUS PARADISI SEED 0.03 mL/50 mL; WATER 98.97 mL/50 mL

KIDNEY STONE CLEAR

PURPOSE

Helps dissolve and clear kidney stones

INDICATIONS AND USAGE

Indications: Homeopathic remedy soothes acute symptoms of kidney stones.

DOSAGE AND ADMINISTRATION

Dosage: Mix 10-15 drops in ¼ cup of water and sip slowly. Repeat every 2 hours until symptoms subside and 3 times daily for 3 days thereafter. May be used with Kidney Dr.™ for long-term kidney health.

GENERAL PRECAUTIONS

Caution: Consult your doctor if symptoms persist or worsen. Keep this and all medications out of reach of children.

ACTIVE INGREDIENT

Ingredients: Each dose contains equal parts of Berberis vulg (6C) (HPUS), Calc carb (6C) (HPUS), Cantharis (6C) (HPUS), Lycopodium (6C) (HPUS), Belladonna (6C) (HPUS)

Citricidal extract (inactive ingredient).

PREGNANCY

If pregnant or breastfeeding, ask a health professional before use.

WARNINGS

Contains no animal products, gluten, artificial flavors, preservatives or colorants. Suitable for vegetarians and safe for all ages.

PATIENT COUNSELING INFORMATION

All Native Remedies health products are especially formulated by experts in the field of natural health and are manufactured according to the highest pharmaceutical standards for maximum safety and effectiveness. For more information, visit us at www.nativeremedies.com

Distributed by

Native Remedies, LLC

6531 Park of Commerce Blvd.

Suite 160

Boca Raton, FL 33487

Phone: 1.877.289.1235

International: + 1.561.999.8857

The letters HPUS indicate that the component(s) in this product is (are) officially monographed in the Homeopathic Pharmacopoeia of the United States.

KEEP OUT OF REACH OF CHILDREN

Keep this and all medications out of reach of children.